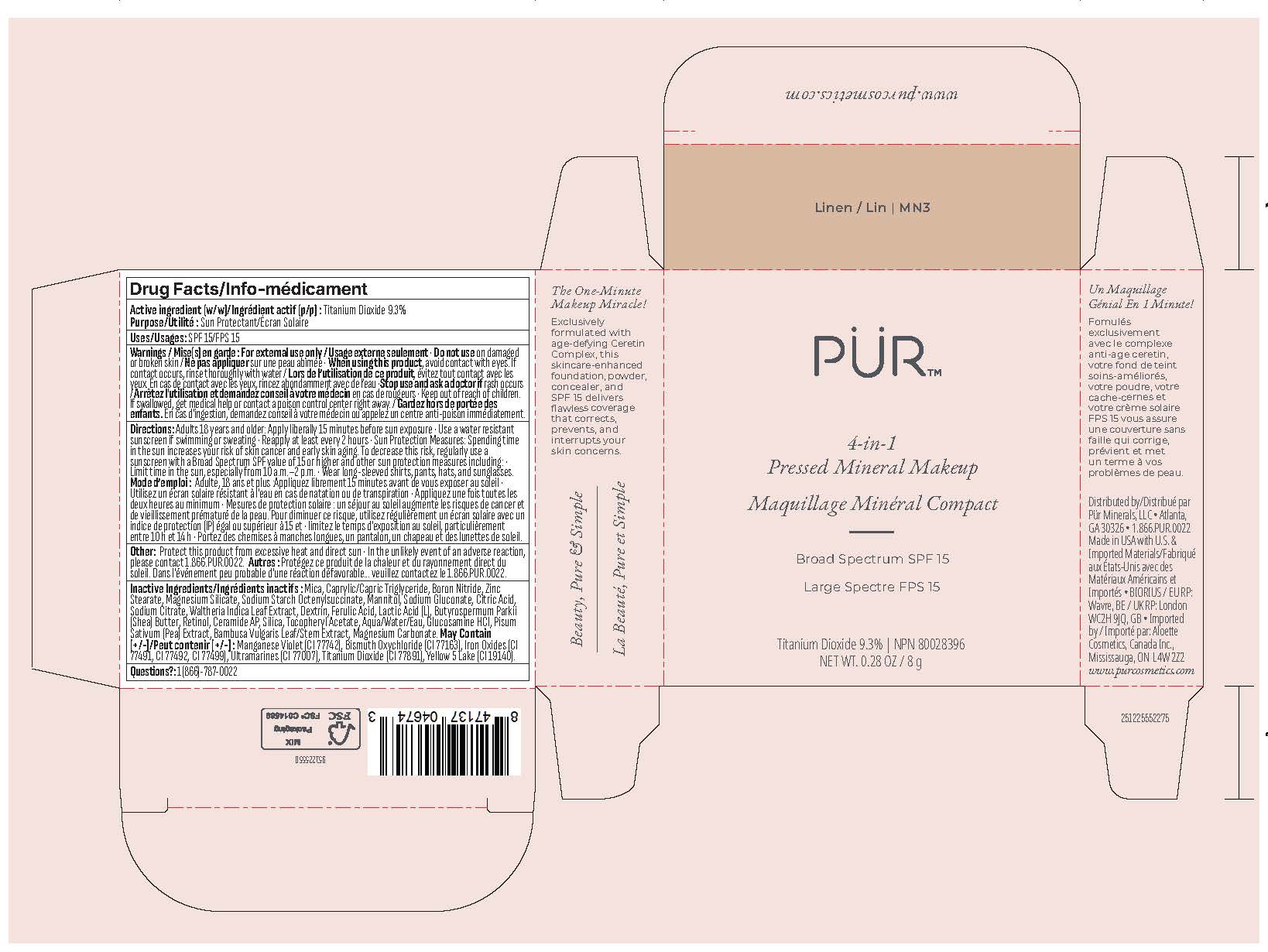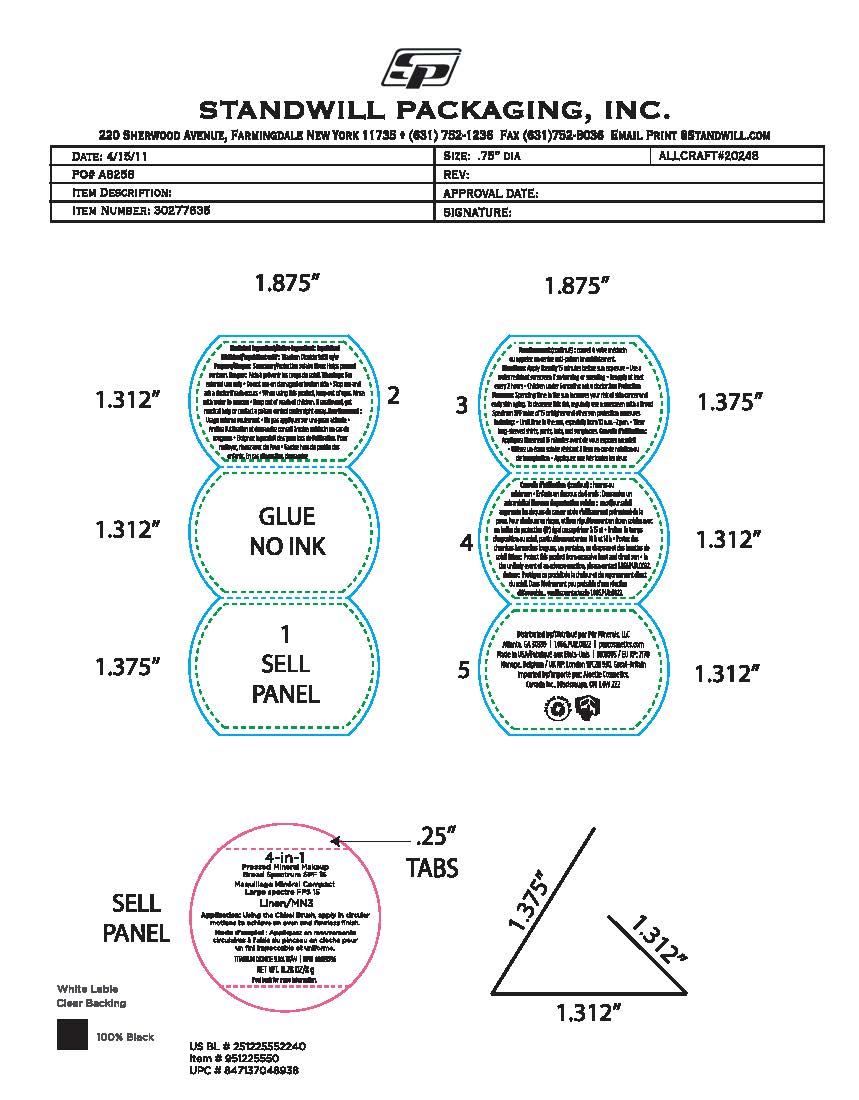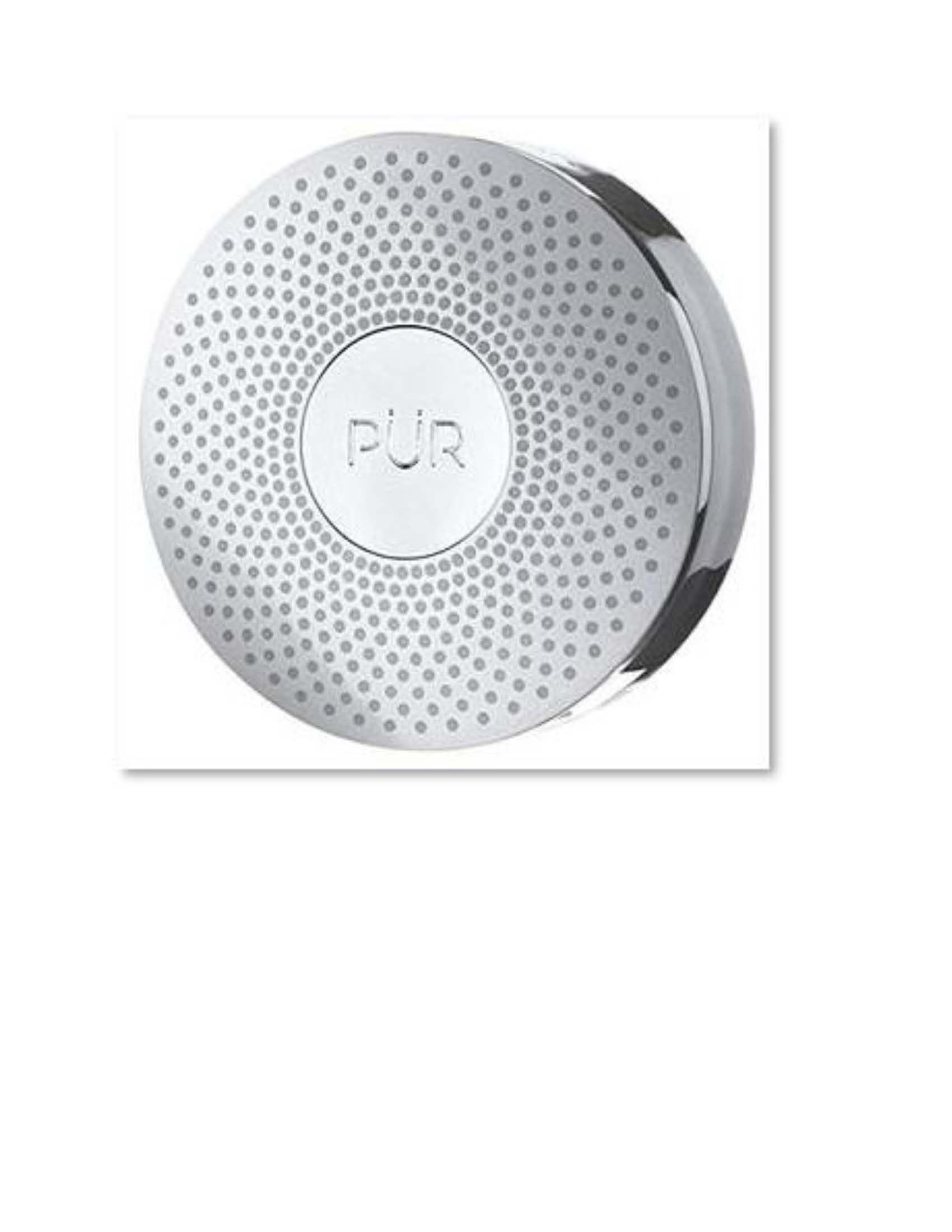 DRUG LABEL: Powder
NDC: 61354-117 | Form: POWDER
Manufacturer: Oxygen Development LLC
Category: otc | Type: HUMAN OTC DRUG LABEL
Date: 20250905

ACTIVE INGREDIENTS: FERRIC OXIDE RED 1.75 mg/100 mg; TITANIUM DIOXIDE 10 mg/100 mg
INACTIVE INGREDIENTS: MAGNESIUM SILICATE 2 mg/100 mg; MANNITOL 1.67 mg/100 mg; BORON NITRIDE 8 mg/100 mg; ZINC STEARATE 2.8 mg/100 mg; SILICON DIOXIDE 0.5 mg/100 mg; SODIUM STARCH GLYCOLATE TYPE A 1.89 mg/100 mg; MICA 51.05 mg/100 mg; BISMUTH OXYCHLORIDE 10 mg/100 mg; MEDIUM-CHAIN TRIGLYCERIDES 8 mg/100 mg

PUR 4-in-1 Pressed Mineral Makeup - LINEN MN3

Active Ingredient

Titanium Dioxide

Purpose

Sunscreen

Uses

Helps prevent sunburn.

Warnings

For external use only

• Do not use on damaged or broken skin

When using

When using this product, keep out of eyes. Rinse with water to remove

• Keep out of reach of children. If swallowed, get medical help or contact a poison control center right away.

Directions

Apply liberally 15 minutes before sun exposure • Use a water resistant sunscreen if swimming or sweating • Reapply at least every 2 hours • Children under 6 months: ask a doctor

Other Information

Protect this product from excessive heat and direct sun • In the unlikely event of an adverse reaction, please contact 1.866.PUR.0022.

Inactive Ingredient

Mica, Caprylic/Capric Triglyceride, Boron Nitride, Bismuth Oxychloride, Zinc Stearate, Magnesium Silicate, Sodium Starch Octenylsuccinate, Mannitol, Sodium Gluconate, Citric Acid, Sodium Citrate, Waltheria Indica Leaf Extract, Dextrin, Ferulic Acid, Lactic Acid (L), Butyrospermum Parkii (Shea) Butter, Retinol, Ceramide AP, Silica, Tocopheryl Acetate, Aqua, Glucosamine HCI, Pisum Sativum (Pea) Extract, Bambusa Vulgaris Leaf/Stem Extract, Magnesium Carbonate, Iron Oxides (CI 77491, CI 77492, CI 77499), May Contain: Titanium Dioxide (CI 77891), Ultramarines (CI 77007).